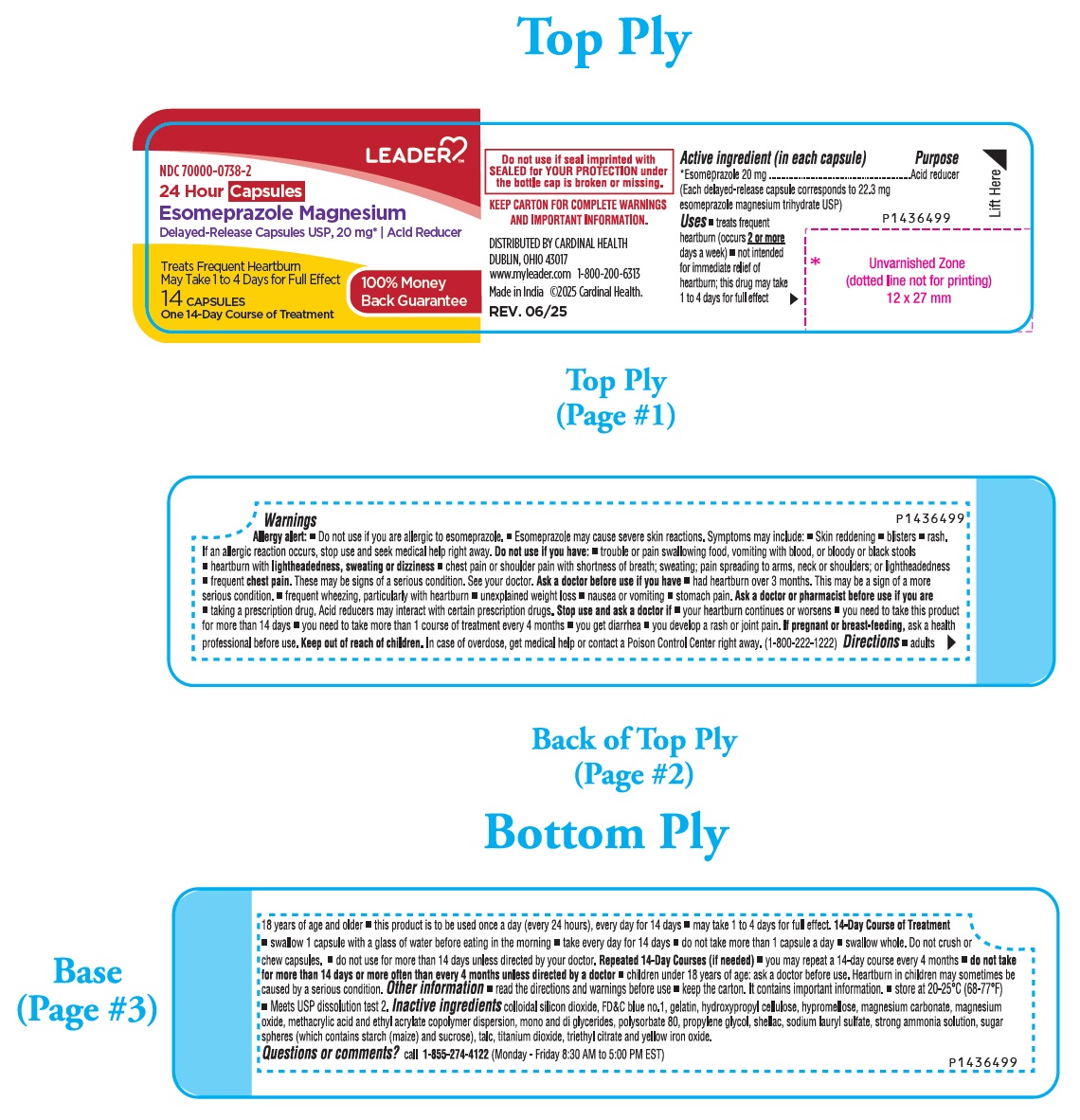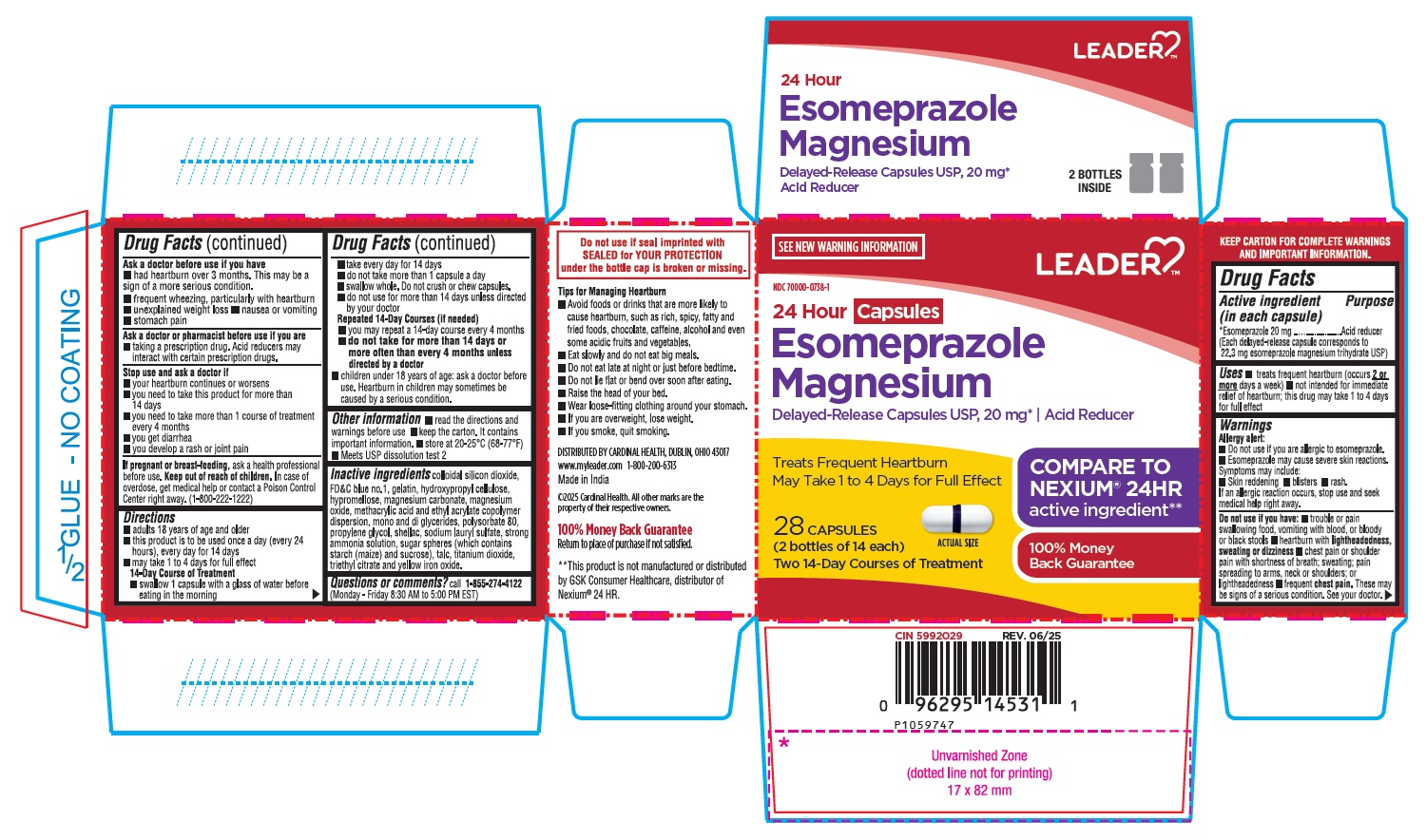 DRUG LABEL: Esomeprazole Magnesium
NDC: 70000-0738 | Form: CAPSULE, DELAYED RELEASE
Manufacturer: LEADER/ CARDINAL HEALTH 110, INC.
Category: otc | Type: Human OTC Drug Label
Date: 20251118

ACTIVE INGREDIENTS: ESOMEPRAZOLE MAGNESIUM TRIHYDRATE 20 mg/1 1
INACTIVE INGREDIENTS: SILICON DIOXIDE; FD&C BLUE NO. 1; GELATIN, UNSPECIFIED; HYDROXYPROPYL CELLULOSE, UNSPECIFIED; HYPROMELLOSE, UNSPECIFIED; MAGNESIUM CARBONATE; MAGNESIUM OXIDE; METHACRYLIC ACID - ETHYL ACRYLATE COPOLYMER (1:1) TYPE A; GLYCERYL MONOSTEARATE; POLYSORBATE 80; PROPYLENE GLYCOL; SHELLAC; SODIUM LAURYL SULFATE; AMMONIA; STARCH, CORN; SUCROSE; TALC; TITANIUM DIOXIDE; TRIETHYL CITRATE; FERRIC OXIDE YELLOW

Esomeprazole Magnesium Delayed-Release Capsules USP 20 mg*

Drug Facts

Active ingredient (in each capsule)

*Esomeprazole 20 mg
(Each delayed-release capsule corresponds to 22.3 mg esomeprazole magnesium trihydrate USP)

Purpose

Acid reducer

Uses

- treats frequent heartburn (occurs 2 or more days a week)
- not intended for immediate relief of heartburn; this drug may take 1 to 4 days for full effect

Warnings

Allergy alert:

- Do not use if you are allergic to esomeprazole.
- Esomeprazole may cause severe skin reactions.

Symptoms may include:

- Skin reddening
- blisters
- rash. If an allergic reaction occurs, stop use and seek medical help right away.

Do not use if you have:

- trouble or pain swallowing food, vomiting with blood, or bloody or black stools
- heartburn with lightheadedness, sweating or dizziness
- chest pain or shoulder pain with shortness of breath; sweating; pain spreading to arms, neck or shoulders; or lightheadedness
- frequent chest pain.

These may be signs of a serious condition. See your doctor.

Ask a doctor before use if you have

- had heartburn over 3 months. This may be a sign of a more serious condition.
- frequent wheezing, particularly with heartburn
- unexplained weight loss
- nausea or vomiting
- stomach pain

Ask a doctor or pharmacist before use if you are

- taking a prescription drug. Acid reducers may interact with certain prescription drugs.

Stop use and ask a doctor if

- your heartburn continues or worsens
- you need to take this product for more than 14 days
- you need to take more than 1 course of treatment every 4 months
- you get diarrhea
- you develop a rash or joint pain

If pregnant or breast-feeding, ask a health professional before use.

Keep out of reach of children.

In case of overdose, get medical help or contact a Poison Control Center right away. (1-800-222-1222)

Directions

- adults 18 years of age and older
- this product is to be used once a day (every 24 hours), every day for 14 days
- may take 1 to 4 days for full effect

14-Day Course of Treatment

- swallow 1 capsule with a glass of water before eating in the morning
- take every day for 14 days
- do not take more than 1 capsule a day
- swallow whole. Do not crush or chew capsules.
- do not use for more than 14 days unless directed by your doctor

Repeated 14-Day Courses (if needed)

- you may repeat a 14-day course every 4 months
- do not take for more than 14 days or more often than every 4 months unless directed by a doctor
- children under 18 years of age: ask a doctor before use. Heartburn in children may sometimes be caused by a serious condition.

Other information

- read the directions and warnings before use
- keep the carton. It contains important information.
- store at 20-25°C (68-77°F)
- Meets USP dissolution test 2

Inactive ingredients

colloidal silicon dioxide, FD&C blue no.1, gelatin, hydroxypropyl cellulose, hypromellose, magnesium carbonate, magnesium oxide, methacrylic acid and ethyl acrylate copolymer dispersion, mono and di glycerides, polysorbate 80, propylene glycol, shellac, sodium lauryl sulfate, strong ammonia solution, sugar spheres (which contains starch (maize) and sucrose), talc, titanium dioxide, triethyl citrate and yellow iron oxide.
Questions or comments?
call 1-855-274-4122 (Monday – Friday 8:30 AM to 5:00 PM EST)

DISTRIBUTED BY CARDINAL HEALTH,
DUBLIN, OHIO 43017
www.myleader.com 1-800-200-6313

Made in India

PACKAGE LABEL-PRINCIPAL DISPLAY PANEL - 20 mg (14 Capsule Container Label)

LEADER™
NDC 70000-0738-2

24 Hour Capsules
Esomeprazole Magnesium
Delayed-Release Capsules USP, 20 mg* | Acid Reducer

Treats Frequent Heartburn May Take 1 to 4 Days for Full Effect

100% Money
Back Guarantee

14 CAPSULES
One 14-Day Course of Treatment

PACKAGE LABEL-PRINCIPAL DISPLAY PANEL - 20 mg (28 Capsule Container Carton Label)

SEE NEW WARNING INFORMATION

LEADER™
NDC 70000-0738-1

24 Hour Capsules
Esomeprazole
Magnesium

Delayed-Release Capsules USP, 20 mg* | Acid Reducer

COMPARE TO

NEXIUM® 24HR
active ingredient**

Treats Frequent Heartburn
May Take 1 to 4 Days for Full Effect

28 CAPSULES

(2 bottles of 14 each)
Two 14-Day Courses of Treatment

Actual Size

100% Money

Back Guarantee